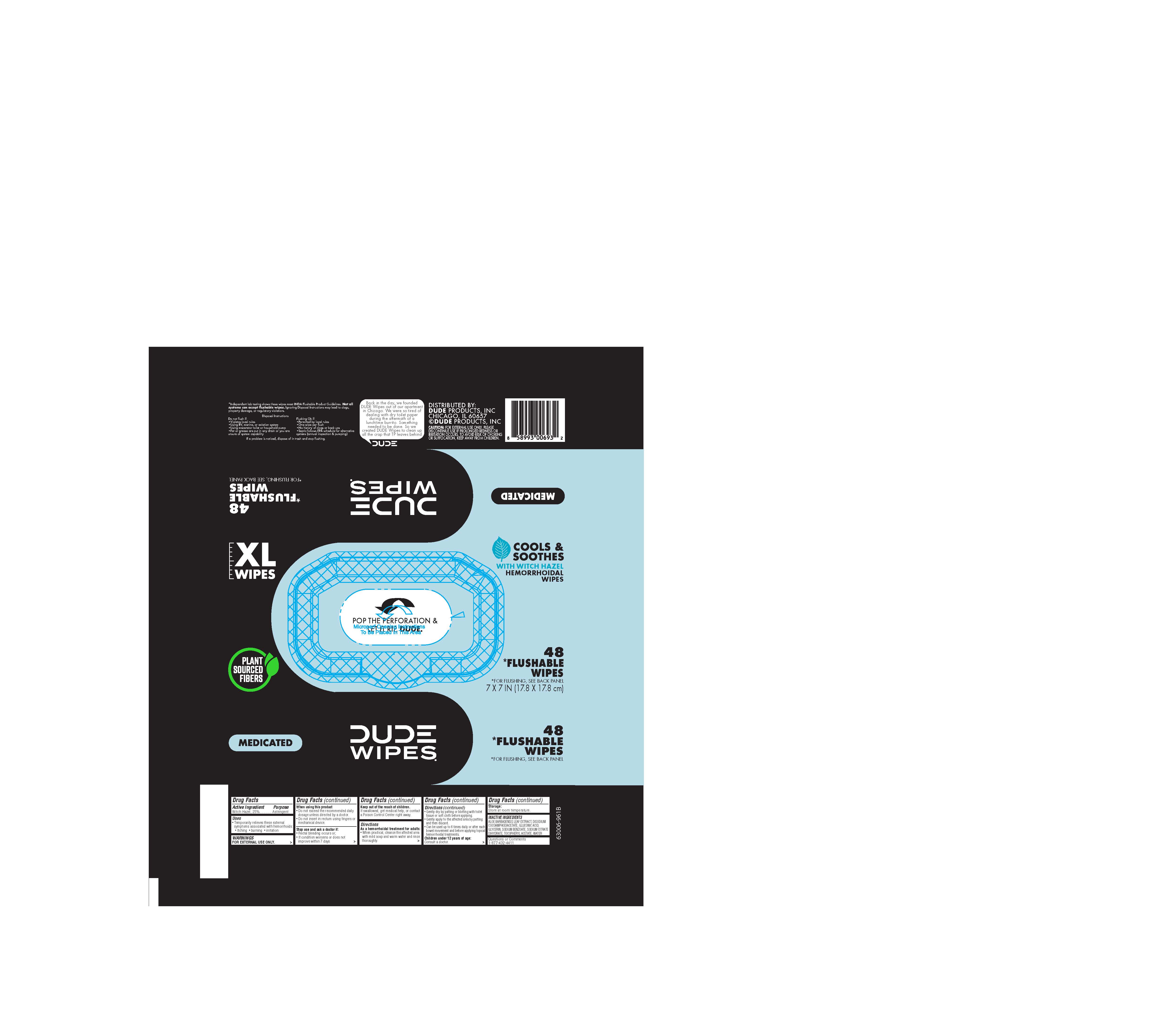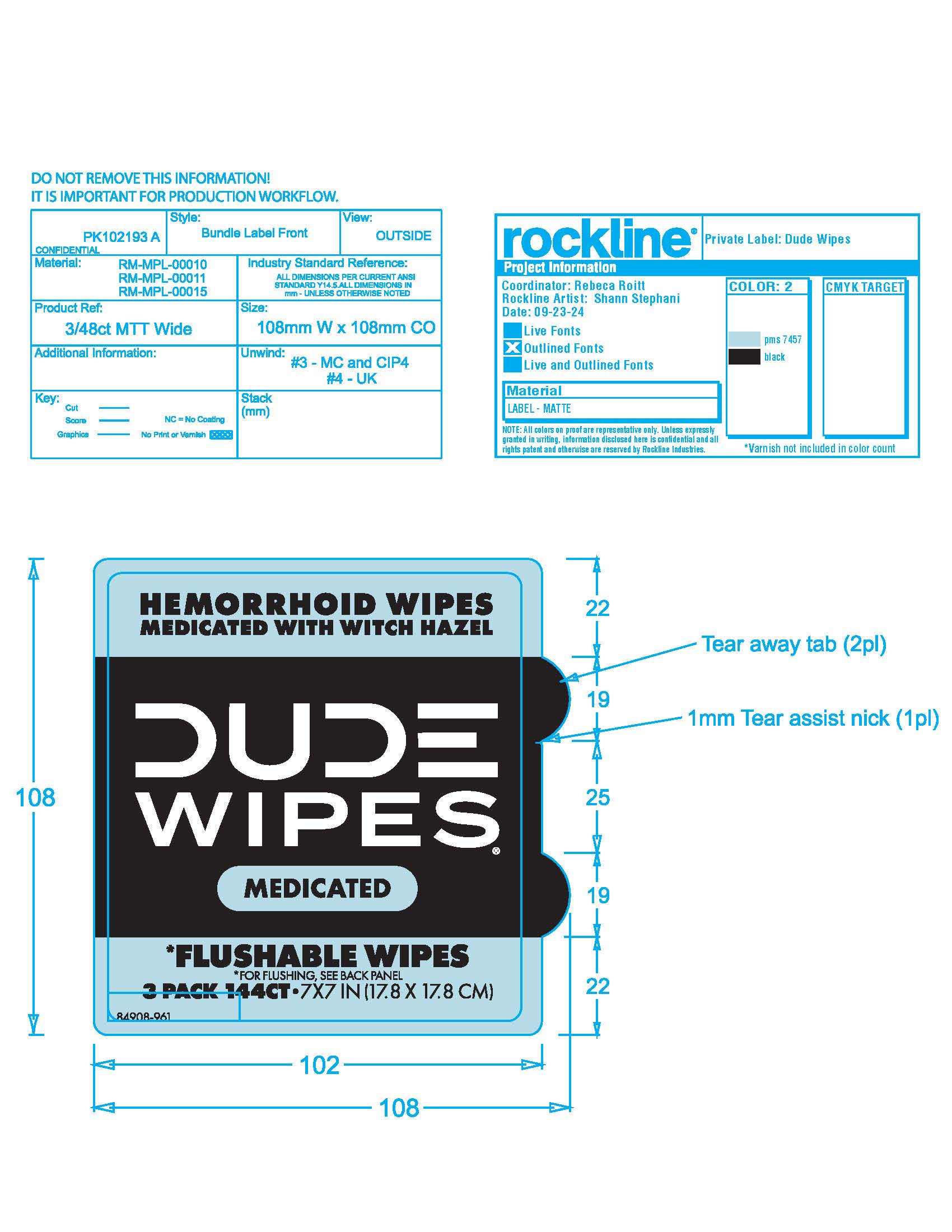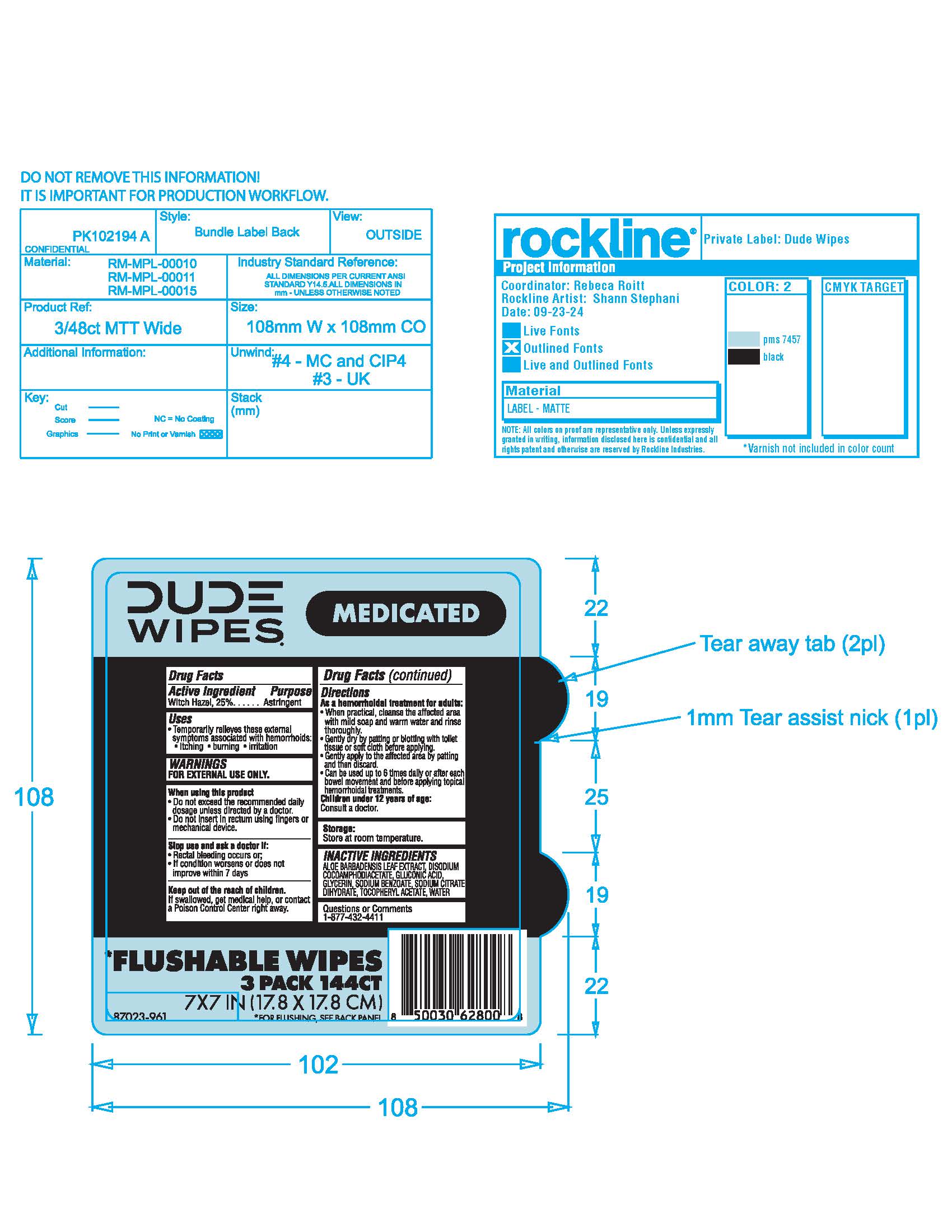 DRUG LABEL: Dude Hemorrhoidal Wipes
NDC: 83731-055 | Form: CLOTH
Manufacturer: Dude Products
Category: otc | Type: HUMAN OTC DRUG LABEL
Date: 20251003

ACTIVE INGREDIENTS: WITCH HAZEL 1.5 g/1 1
INACTIVE INGREDIENTS: GLUCONIC ACID; ALOE VERA LEAF; .ALPHA.-TOCOPHEROL ACETATE; WATER; DISODIUM COCOAMPHODIACETATE; SODIUM BENZOATE; TRISODIUM CITRATE DIHYDRATE; GLYCERIN

DUDE Hemorrhoidal Wipes

Active Ingredient

Witch Hazel 25%

Purpose

Astringent

Uses

• Temporarily relieves these external symptoms associated with hemorrhoids:
• Itching • burning • irritation

Warnings

For external use only

When using this product

• Do not exceed the recommended daily dosage unless directed by a doctor.

• Do not insert in rectum using ﬁngers or mechanical device.

Stop use and ask a doctor if

• Rectal bleeding occurs or;

• If condition worsens or does not improve within 7 days

Keep out of reach of children

if swallowed, get medical help, or contact a Poison Control Center right away.

Directions

As a hemorrhoidal treatment for adults:

• When practical, cleanse the affected area with mild soap and warm water and rinse thoroughly.

• Gently dry by patting or blotting with toilet tissue or soft cloth before applying.
• Gently apply to the affected area by patting and then discard.
Children under 12 years of age: Consult a doctor

Dosage

Can be used up to 6 times daily or after each bowel movement and before applying topical hemorrhoidal treatments.

Storage

Storage: Store at room temperature.

Inactive ingredients

ALOE BARBADENSIS LEAF EXTRACT, DISODIUM COCOAMPHODIACETATE, GLUCONIC ACID, GLYCERIN, SODIUM BENZOATE, SODIUM CITRATE DIHYDRATE, TOCOPHERYL ACETATE, WATER

Questions or Comments

1-877-432-4411